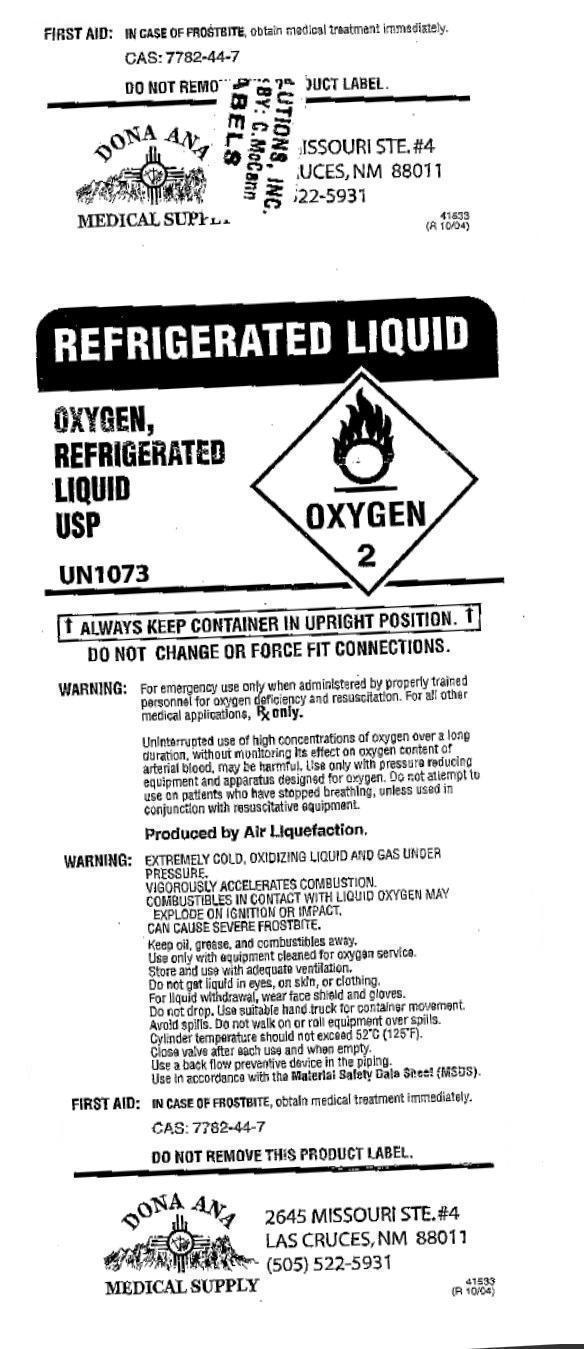 DRUG LABEL: OXYGEN, REFRIGERATED 
                
NDC: 42545-000 | Form: GAS
Manufacturer: Dona Ana Medical Supply DBA Silver City Medical Supply
Category: prescription | Type: HUMAN PRESCRIPTION DRUG LABEL
Date: 20150618

ACTIVE INGREDIENTS: OXYGEN 1 L/1 L

OXYGEN, REFRIGERATED LIQUID USP

OXYGEN, REFRIGERATED LIQUID USP (42545-000-00

FIRST AID: IN CASE OF FROSTBITE, obtain medical treatment immediately.

CAS: 7782-44-7

DO NOT REMOVE PRODUCT LABEL.

DONA ANA MEDICAL SUPPLY

2645 MISSOURI STE. 4

LAS CRUCES, NM 88011

(505) 522-5931

REFRIGERATED LIQUID

OXYGEN,

REFRIGERATED

LIQUID

USP

UN1073

ALWAYS KEEP CONTAINER IN UPRIGHT POSITION

DO NOT CHANGE OR FORCE FIT CONNECTIONS

WARNING: For emergency use only when administered by properly trained personnel for oxygen deficiency and resuscitation. For all other medical applications, Rx only.

Uninterrupted use of high concentrations of oxygen over a long duration, without monitoring its effect on oxygen content of arterial blood, may be harmful. Use only with pressure reducing equipment and apparatus designed for

oxygen. Do not attempt to use on patients who have stopped breathing, unless used in conjunction with resuscitative equipment.

PRODUCED BY AIR LIQUEFACTION

WARNING: EXTREMELY COLD, OXIDIZING LIQUID AND GAS UNDER PRESSURE.

VIGOROUSLY ACCELERATES COMBUSTION.

COMBUSTIBLE IN CONTACT WITH LIQUID OXYGEN MAY EXPLODE ON IGNITION OR IMPACT/

CAN CAUSE SEVERE FROSTBITE.

Keep oil, grease and combustibles away.

Use only with equipment cleaned for oxygen service. Store and use with adequate ventilation. Do not get liquid in eyes, on skin, or clothing. For liquid withdrawal, wear face shield and gloves. Do not drop. Use suitable hand truck for

container movement. Avoid spills. Do not walk on or roll equipment over spills. Cylinder temperature should not exceed 52 degrees C (125 degrees F). Close valve after each use and when empty. Use a back flow preventive device

in the piping. Use in accordance with the Material Safety Data Sheet (MSDS).